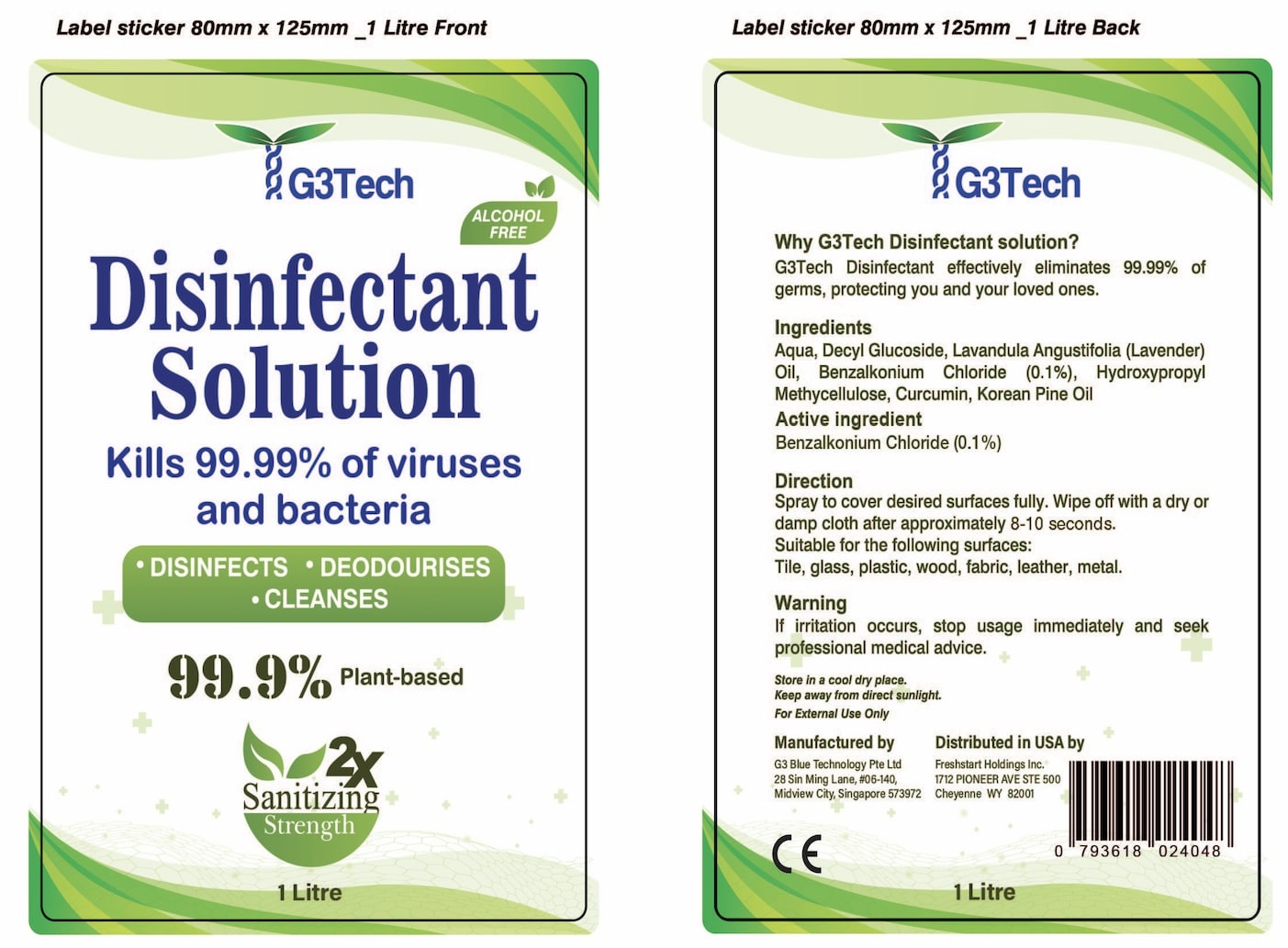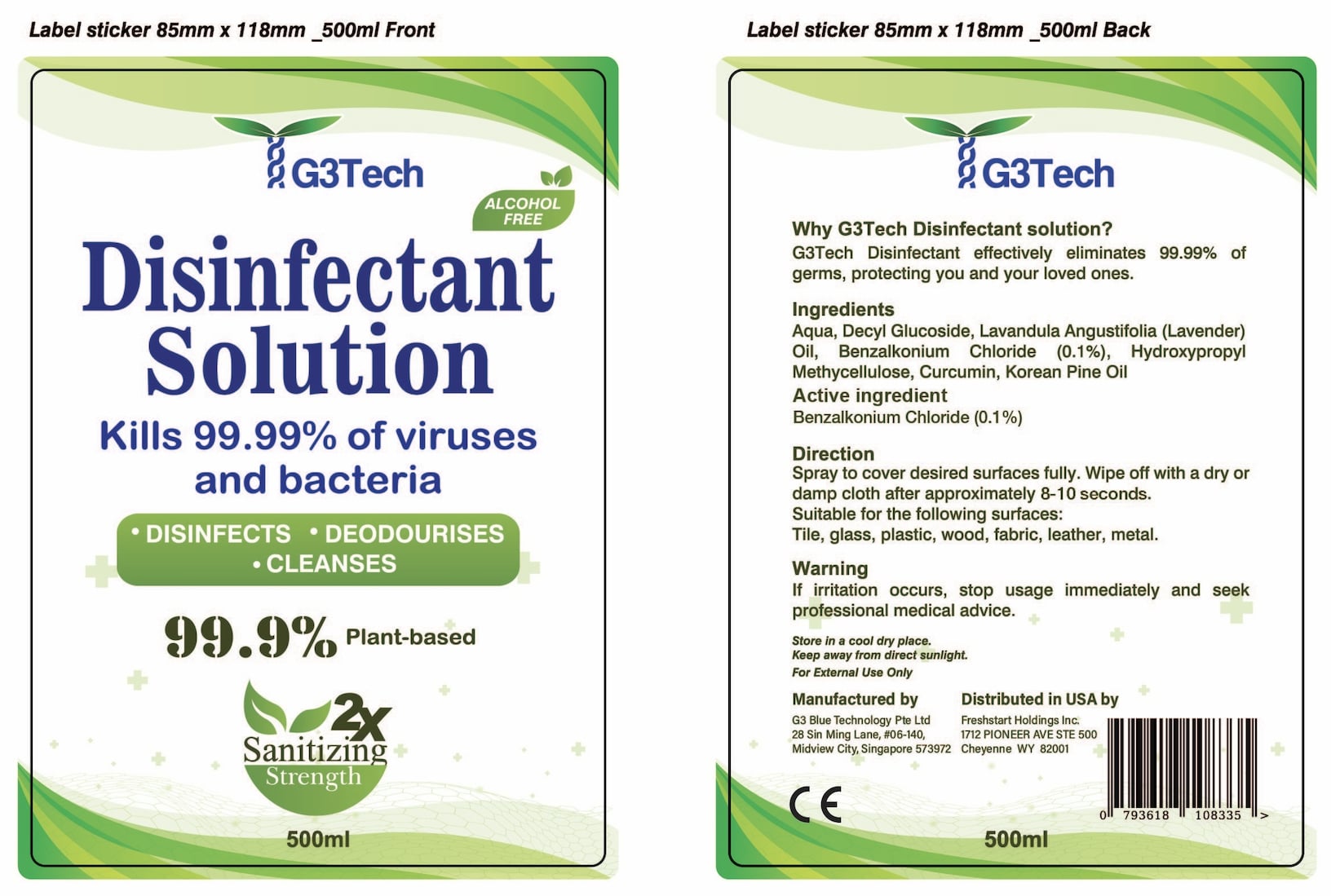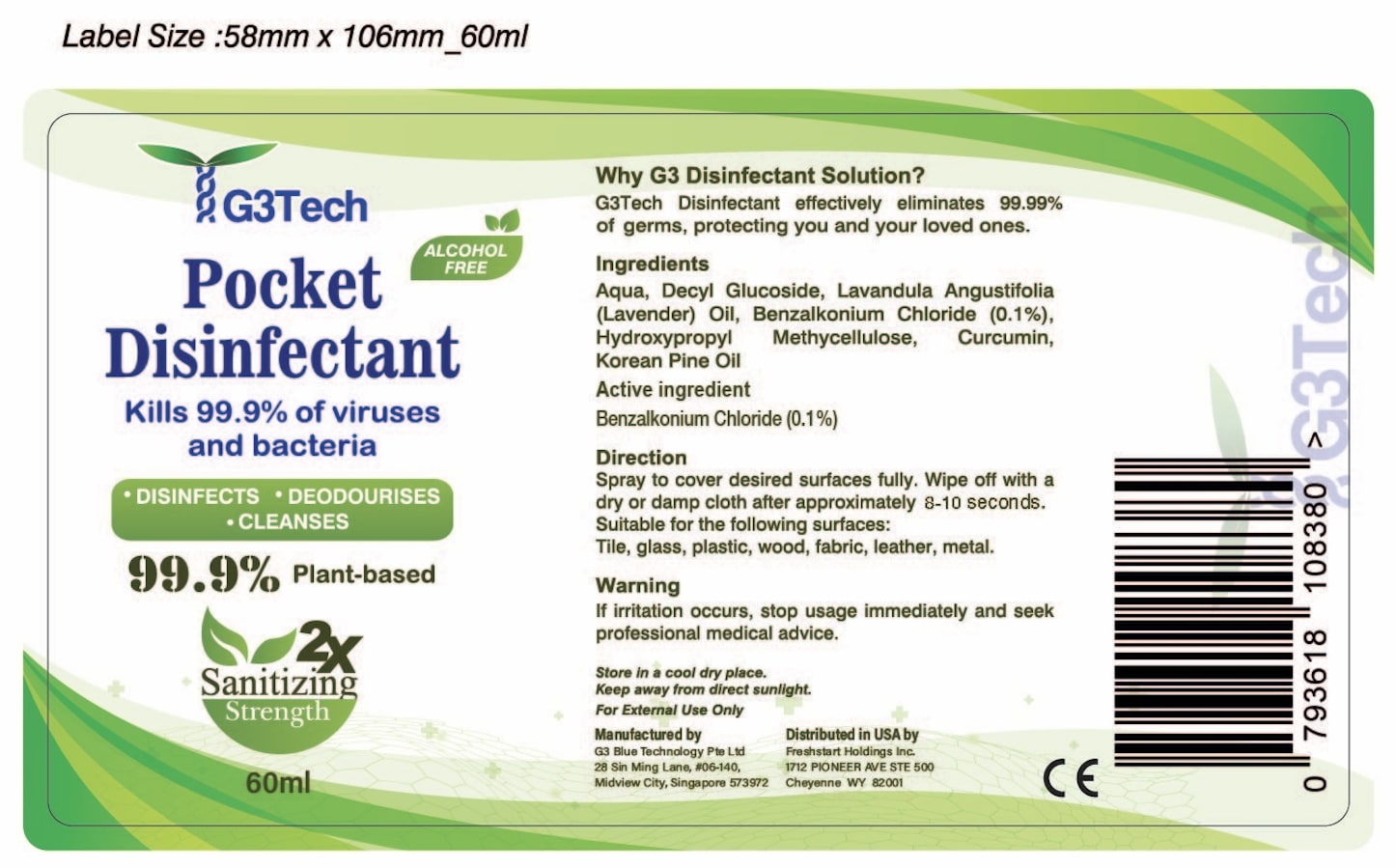 DRUG LABEL: G3Tech Disinfectant
NDC: 79176-003 | Form: AEROSOL, SPRAY
Manufacturer: Freshstart Holdings Inc.
Category: otc | Type: HUMAN OTC DRUG LABEL
Date: 20200917

ACTIVE INGREDIENTS: BENZALKONIUM CHLORIDE 1000 mg/1 mL
INACTIVE INGREDIENTS: DECYL GLUCOSIDE; GLYCERIN; WATER; LAVENDER OIL; WHITE PINE OIL; HYPROMELLOSE, UNSPECIFIED; CURCUMIN

Active Ingredient(s)

Benzalkonium Chloride 0.1% v/v. Purpose: Antiseptic

Purpose

Antiseptic, Topical

Use

Disinfectant spray to help reduce bacteria that help protect against infection on skin and surfaces.

Warnings

For External Use Only.

Directions

Spray to cover desired surfaces fully

Wipe off with a dry or damp cloth after approximately 8-10 seconds

Suitable for the following surfaces:

Tile, glass, plastic, wood, fabric, leather, metal

Other information

- Store in a cool dry place
- Keep away from direct sunlight

Inactive ingredients

Aqua

Decyl Glucoside

Lavandula Angustifolia (Lavender) Oil

Hydroxypropyl Methycellulose

Curcumin

Korean Pine Oil

Keep out of reach of children.

Package Label - Principal Display Panel

60ml NDC: 80062-003-01

500ml NDC: 80062-003-02

1000ml NDC: 80062-003-03